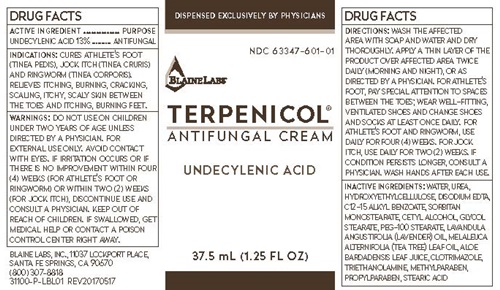 DRUG LABEL: TERPENICOL
NDC: 63347-601 | Form: CREAM
Manufacturer: Blaine Labs Inc.
Category: otc | Type: HUMAN OTC DRUG LABEL
Date: 20231221

ACTIVE INGREDIENTS: UNDECYLENIC ACID 4.55 g/37.5 mL
INACTIVE INGREDIENTS: WATER; UREA; HYDROXYETHYL CELLULOSE (140 CPS AT 5%); EDETATE DISODIUM; ALKYL (C12-15) BENZOATE; POLYSORBATE 80; SORBITAN MONOLAURATE; CETYL ALCOHOL; GLYCOL STEARATE; PEG-100 STEARATE; LAVENDER OIL; TEA TREE OIL; ALOE VERA LEAF; CLOTRIMAZOLE; TROLAMINE; METHYLPARABEN; PROPYLPARABEN

Terpenicol - 601

DRUG FACTS ACTIVE INGREDIENT

UNDECYLENIC ACID 13%

PURPOSE

ANTIFUNGAL

KEEP OUT OF REACH OF CHILDREN. IF SWALLOWED, GET MEDICAL HELP OR CONTACT A POISON CONTROL CENTER RIGHT AWAY.

INDICATIONS:

CURES ATHLETE'S FOOT (TINEA PEDIS), JOCK ITCH (TINA CRURIS) AND RINGWORM (TINA CORPORIS). RELIEVES ITCHING, BURNING, CRACKING, SCALING, ITCHY, SCALY BETWEEN TOES AND ITCHING, BURNING FEET.

WARNINGS:

DO NOT USE ON CHILDREN UNDER TWO YEARS OF AGE UNLESS DIRECTED BY A PHYSICIAN. FOR EXTERNAL USE ONLY. AVOID CONTACT WITH EYES. IF IRRITATION OCCURS OR IF THERE IS NOT IMPROVEMENT WITHIN FOUR (4) WEEKS (FOR ATHLETE'S FOOT OR RINGWORM) OR WITHIN TWO (2) WEEKS (FOR JOCK ITCH), DISCONTINUE USE AND CONSULT A PHYSICIAN.

DIRECTIONS:

WASH THE AFFECTED AREA WITH SOAP AND WATER AND DRY THOROUGHLY. APPLY A THIN LAYER OF THE PRODUCT OVER AFFECTED AREA TWICE DAILY (MORNING AND NIGHT), OR AS DIRECTED BY A PHYSICIAN. FOR ATHLETE'S FOOT, PAY SPECIAL ATTENTION TO SPACES BETWEEN THE TOES; WEAR WELL-FITTING, VENTILATED SHOES AND CHANGE SHOES AND SOCKS AT LEAST ONCE DAILY. FOR ALHTLETE'S FOOT AND RINGWORM, USE DAILY FOR FOUR (4) WEEKS. FOR JOCK ITCH, USE DAILY FOR TWO (2) WEEKS. IF CONDITION PERSISTS LONGER, CONSULT A PHYSICIAN. WASH HANDS AFTER EACH USE.

INACTIVE INGREDIENTS:

WATER, UREA, HYDROXYETHYLCELLULOSE, DISODIUM EDTA, C12-15 ALKYL BENZOATE, POLYSORBATE 80, SORBITAN LAURATE, CETYL ALCOHOL,
GLYCOL STEARATE, PEG-100 STEARATE, LAVANDULA ANGUSTIFOLIA (LAVENDER) OIL, MELALEUCA ALTERNIFOLIA (TEA TREE) LEAF OIL, ALOE BARDADENSIS LEAF JUICE, CLOTRIMAZOLE, TRIETHANOLAMINE, METHYLPARABEN, PROPYLPARABEN

TERPENICOL ANTIFUNGAL CREAM PRODUCT LABEL

DISPENSED EXCLUSIVELY BY PHYSICIANS

NDC-601-01

BLAINE LABS®

TERPENICOL®
ANTIFUNGAL CREAM

UNDECYLENIC ACID

37.5 mL (1.25 FL OZ)

BLAINE LABS, INC., 11037 LOCKPORT PLACE,
SANTA FE SPRINGS, CA 90670
(800) 307-8818
31100-P-LBL01 REV20170517

res